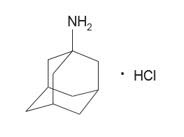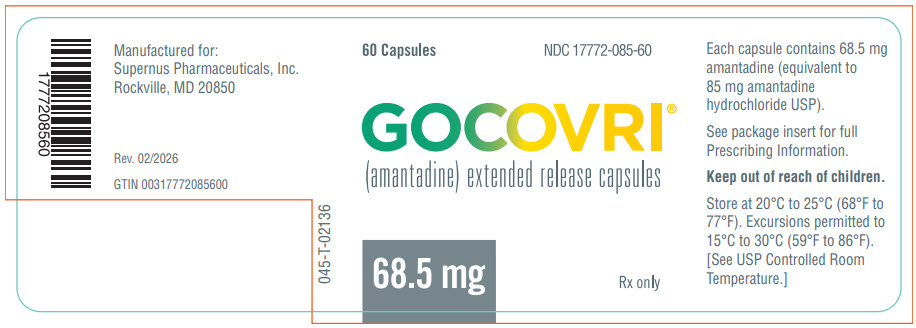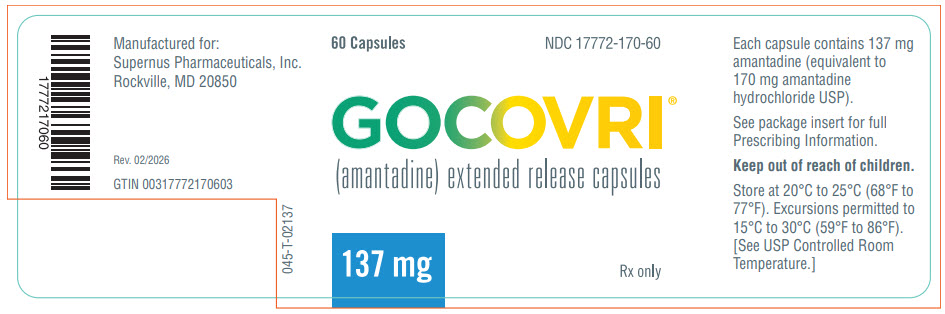 DRUG LABEL: GOCOVRI
NDC: 17772-085 | Form: CAPSULE, COATED PELLETS
Manufacturer: Supernus Pharmaceuticals
Category: prescription | Type: HUMAN PRESCRIPTION DRUG LABEL
Date: 20260216

ACTIVE INGREDIENTS: AMANTADINE 68.5 mg/1 1
INACTIVE INGREDIENTS: COPOVIDONE K25-31 5.66 mg/1 1; ETHYLCELLULOSE (7 MPA.S) 31.06 mg/1 1; HYPROMELLOSE 2910 (3 MPA.S) 12.89 mg/1 1; MAGNESIUM STEARATE 0.2 mg/1 1; MEDIUM-CHAIN TRIGLYCERIDES 3.75 mg/1 1; MICROCRYSTALLINE CELLULOSE 24.29 mg/1 1; POVIDONE K90 4.2 mg/1 1; TALC 5.54 mg/1 1

HIGHLIGHTS OF PRESCRIBING INFORMATION

These highlights do not include all the information needed to use GOCOVRI® safely and effectively. See full prescribing information for GOCOVRI®.
GOCOVRI® (amantadine) extended-release capsules, for oral use
Initial U.S. Approval: 1968

RECENT MAJOR CHANGES

Warnings and Precautions (5.6) | 7/2025

1 INDICATIONS AND USAGE

GOCOVRI®is indicated:

- For the treatment of dyskinesia in patients with Parkinson's disease receiving levodopa-based therapy, with or without concomitant dopaminergic medications (1)
- As adjunctive treatment to levodopa/carbidopa in patients with Parkinson's disease experiencing "off" episodes (1)

2 DOSAGE AND ADMINISTRATION

- Administer orally once daily at bedtime (2.1, 2.3)
- The initial daily dosage is 137 mg; after 1 week, increase to the recommended daily dosage of 274 mg (2.1)
- Swallow whole; may sprinkle contents on soft food (2.2)
- May be taken with or without food; avoid use with alcohol (2.2)
- A lower dosage is recommended for patients with moderate or severe renal impairment (2.3)

3 DOSAGE FORMS AND STRENGTHS

Extended-release capsules: 68.5 mg and 137 mg (3)

4 CONTRAINDICATIONS

GOCOVRI is contraindicated in patients with end-stage renal disease (4)

5 WARNINGS AND PRECAUTIONS

- Falling Asleep During Activities of Daily Living: Advise patients prior to treatment; ordinarily discontinue if occurs (5.1)
- Suicidality and Depression: Monitor patients for depressed mood, depression, or suicidal ideation or behavior (5.2)
- Hallucinations/Psychotic Behavior: Patients with major psychotic disorder should ordinarily not be treated with GOCOVRI; observe patients for the occurrence of hallucinations throughout treatment, especially at initiation and after dose increases (5.3)
- Dizziness and Orthostatic Hypotension: Monitor patients for dizziness and orthostatic hypotension, especially after starting GOCOVRI or increasing the dose (5.4)
- Withdrawal-Emergent Hyperpyrexia and Confusion: Avoid sudden discontinuation (5.5)
- Corneal Edema: Monitor patients for new changes in vision, including blurred vision, with or without eye pain, or vision loss. Taper and discontinue if corneal edema occurs (5.6)
- Impulse Control/Compulsive Behaviors: Ask patients about increased gambling urges, sexual urges, uncontrolled spending or other urges; consider dose reduction or discontinuation if occurs (5.7)

6 ADVERSE REACTIONS

The most commonly observed adverse reactions occurring at a frequency of >10% and greater than placebo were hallucination, dizziness, dry mouth, peripheral edema, constipation, fall, and orthostatic hypotension (6.1)

To report SUSPECTED ADVERSE REACTIONS, contact Supernus Pharmaceuticals, Inc. at 1-833-223-2627 or FDA at 1-800-FDA-1088 or http://www/fda.gov/medwatch.

7 DRUG INTERACTIONS

- Other Anticholinergic Drugs: Doses should be reduced if atropine-like effects occur (7.1)
- Drugs Affecting Urinary pH: Excretion increases with acidic urine; possible accumulation with urine change towards alkaline (7.2)
- Live Attenuated Influenza Vaccines: Not recommended during use (7.3)
- Alcohol: Concomitant use not recommended (7.4)

8 USE IN SPECIFIC POPULATIONS

- Pregnancy: Based on animal data, may cause fetal harm (8.1)

FULL PRESCRIBING INFORMATION

1 INDICATIONS AND USAGE

GOCOVRI®is indicated:

- For the treatment of dyskinesia in patients with Parkinson's disease receiving levodopa-based therapy, with or without concomitant dopaminergic medications
- As adjunctive treatment to levodopa/carbidopa in patients with Parkinson's disease experiencing "off" episodes

2 DOSAGE AND ADMINISTRATION

2.1 Dosing Information

The initial daily dosage of GOCOVRI is 137 mg, administered orally once daily at bedtime. After one week, increase to the recommended dosage of 274 mg (two 137 mg capsules) once daily at bedtime. GOCOVRI is not substitutable with other amantadine immediate- or extended-release products.

2.2 Administration Information

GOCOVRI should be swallowed whole. Do not crush, chew or divide capsules. If needed, GOCOVRI may be administered by carefully opening and sprinkling the entire contents on a small amount (teaspoonful) of soft food, such as applesauce. The drug/food mixture should be swallowed immediately without chewing. Do not store mixture for future use.

GOCOVRI can be taken with or without food [see Clinical Pharmacology (12.3)].

Concomitant use of GOCOVRI with alcohol is not recommended [see Drug Interactions (7.4)].

It is recommended to avoid sudden discontinuation of GOCOVRI [see Dosage and Administration (2.4)].

2.3 Dosing in Patients with Renal Impairment

The initial and maximum recommended daily dosage of GOCOVRI for patients with renal impairment (creatinine clearance estimated by Modification of Diet in Renal Disease (MDRD) method) is provided below.

Creatinine Clearance | Dosage
Mild renal impairment (60 to 89 mL/min/1.73 m^2) | Initial dosage: 137 mg once daily at bedtime. After one week, increase to recommended dosage of 274 mg once daily at bedtime.
Moderate renal impairment (30 to 59 mL/min/1.73 m^2) | Initial dosage: 68.5 mg once daily at bedtime Maximum recommended dosage: 137 mg once daily at bedtime ^1
Severe renal impairment (15 to 29 mL/min/1.73 m^2) | 68.5 mg once daily at bedtime
End Stage Renal Disease (below 15 mL/min/1.73 m^2) | Contraindicated
^1Increase, if needed, after one week of the initial dosage

2.4 Discontinuation and Missed Dose

Rapid dose reduction or withdrawal of GOCOVRI may cause adverse reactions [see Warnings and Precautions (5.5)]. Therefore, to discontinue GOCOVRI in patients who have been on the drug for more than 4 weeks, GOCOVRI dosage should, if possible, be reduced by half for the final week of dosing.

If a dose of GOCOVRI is missed, the next dose should be taken as scheduled.

3 DOSAGE FORMS AND STRENGTHS

GOCOVRI is available as extended-release capsules for oral administration. Each capsule contains 68.5 mg or 137 mg of amantadine.

The 68.5 mg capsule is a white opaque size #2 capsule, with black printing of 'ADAMAS' on front and '85' on back of the cap and three black bands printed on body of capsule.

The 137 mg capsule is a light blue opaque size #0 capsule, with black printing of 'ADAMAS' on front and '170' on back of the cap and three black bands printed on body of capsule.

4 CONTRAINDICATIONS

GOCOVRI is contraindicated in patients with end-stage renal disease (i.e., creatinine clearance below 15 mL/min/1.73 m^2) [see Clinical Pharmacology (12.3)].

5 WARNINGS AND PRECAUTIONS

5.1 Falling Asleep During Activities of Daily Living and Somnolence

Patients treated for Parkinson's disease have reported falling asleep while engaged in activities of daily living, including the operation of motor vehicles, which sometimes has resulted in accidents. Patients may not perceive warning signs, such as excessive drowsiness, or they may report feeling alert immediately prior to the event. In controlled clinical trials, somnolence and fatigue were reported as adverse reactions in 4% of patients treated with GOCOVRI 274 mg and 1% for placebo.

Before initiating treatment with GOCOVRI, advise patients of the potential to develop drowsiness and specifically ask about factors that may increase the risk for somnolence with GOCOVRI, such as concomitant sedating medications or the presence of a sleep disorder. If a patient develops daytime sleepiness or episodes of falling asleep during activities that require full attention (e.g., driving a motor vehicle, conversations, eating), GOCOVRI should ordinarily be discontinued.

If a decision is made to continue GOCOVRI, patients should be advised not to drive and to avoid other potentially dangerous activities. There is insufficient information to establish that dose reduction will eliminate episodes of falling asleep while engaged in activities of daily living or daytime somnolence.

5.2 Suicidality and Depression

In controlled clinical trials, suicidal ideation or suicide attempt was reported in 2% of GOCOVRI-treated patients and 0% of placebo-treated patients. Depression or depressed mood was reported in 6% of GOCOVRI-treated patients and 1% of placebo-treated patients. Confusional state was reported in 3% of GOCOVRI-treated patients and 2% of placebo-treated patients. Apathy was reported in 2% of GOCOVRI-treated patients and 0% of placebo-treated patients.

Monitor patients for depression, including suicidal ideation or behavior. Prescribers should consider whether the benefits outweigh the risks of treatment with GOCOVRI in patients with a history of suicidality or depression.

5.3 Hallucinations/Psychotic Behavior

Patients with a major psychotic disorder should ordinarily not be treated with GOCOVRI because of the risk of exacerbating psychosis. In controlled trials, the incidence of patients who experienced visual hallucinations, auditory hallucinations, delusions, illusions, or paranoia was 25% in patients treated with GOCOVRI 274 mg, and 3% in placebo-treated patients. Hallucinations caused discontinuation of treatment in 8% of GOCOVRI-treated patients, and in 0% of placebo-treated patients.

Observe patients for the occurrence of hallucinations throughout treatment, especially at initiation, and after dose increases.

5.4 Dizziness and Orthostatic Hypotension

In controlled clinical trials, 29% of GOCOVRI-treated patients and 2% of placebo-treated patients experienced dizziness, syncope, orthostatic hypotension, presyncope, postural dizziness or hypotension. In GOCOVRI-treated patients, 3% discontinued study treatment because of dizziness, postural dizziness, or syncope, compared to 0% of placebo-treated patients.

Monitor patients for dizziness and orthostatic hypotension, especially after starting GOCOVRI or increasing the dose. Concomitant use of alcohol when using GOCOVRI is not recommended [see Drug Interactions (7.4)].

5.5 Withdrawal-Emergent Hyperpyrexia and Confusion

A symptom complex resembling neuroleptic malignant syndrome (characterized by elevated temperature, muscular rigidity, altered consciousness, and autonomic instability), with no other obvious etiology, has been reported in association with rapid dose reduction, withdrawal of, or changes in drugs that increase central dopaminergic tone.

Abrupt discontinuation of GOCOVRI may cause an increase in the symptoms of Parkinson's disease or cause delirium, agitation, delusions, hallucinations, paranoid reaction, stupor, anxiety, depression, or slurred speech. It is recommended to avoid sudden discontinuation of GOCOVRI [see Dosing Information (2.4)] .

5.6 Corneal Edema

Corneal edema has been reported in patients taking amantadine. Symptoms include sudden onset of blurry vision, or progressive vision loss, with or without eye pain. Corneal involvement is usually bilateral. Onset can occur from a few weeks to several years after starting amantadine. Resolution of symptoms typically begins within weeks of amantadine cessation. However, corneal grafts have been required in some patients when the condition is not recognized. Permanent damage can occur if amantadine is continued. Ask patients if their vision has changed and obtain ophthalmologic examinations to rule out corneal edema should vision changes occur after initiation of therapy with GOCOVRI. If corneal edema occurs, taper and discontinue GOCOVRI [see Dosage and Administration (2.4)] .

5.7 Impulse Control/Compulsive Behaviors

Patients can experience intense urges to gamble, increased sexual urges, intense urges to spend money, binge eating, and/or other intense urges, and the inability to control these urges while taking one or more of the medications, including GOCOVRI, that increase central dopaminergic tone. In some cases, these urges were reported to have stopped when the dose was reduced or the medication was discontinued. Because patients may not recognize these behaviors as abnormal, it is important for prescribers to specifically ask patients or their caregivers about the development of new or increased gambling urges, sexual urges, uncontrolled spending, or other urges while being treated with GOCOVRI. Consider dose reduction or stopping the medication if a patient develops such urges while taking GOCOVRI.

6 ADVERSE REACTIONS

The following serious adverse reactions are described in more detail elsewhere in the labeling:

- Falling Asleep During Activities of Daily Living and Somnolence [see Warnings and Precautions (5.1)]
- Suicidality and Depression [see Warnings and Precautions (5.2)]
- Hallucinations/Psychotic Behavior [see Warnings and Precautions (5.3)]
- Dizziness and Orthostatic Hypotension [see Warnings and Precautions (5.4)]
- Withdrawal-Emergent Hyperpyrexia and Confusion [see Warnings and Precautions (5.5)]
- Corneal Edema [see Warnings and Precautions (5.6)]
- Impulse Control/Compulsive Behaviors [see Warnings and Precautions (5.7)]

6.1 Clinical Trial Experience

Because clinical trials are conducted under widely varying conditions, adverse reaction rates observed in the clinical trials of a drug cannot be directly compared to rates in the clinical trials of another drug and may not reflect the rates observed in practice.

Placebo-Controlled Trials

GOCOVRI was evaluated in two double-blind, placebo-controlled efficacy trials of similar design and population: Study 1 (123 patients) and Study 2 (75 patients) [see Clinical Studies (14)] . The study population was approximately 56% male and 94% white, with a mean age of 65 years (age range from 34 years to 82 years). The mean duration of levodopa-induced dyskinesia was 4 years (range 0.1 to 14 years). Active treatment started at 137 mg once daily for one week, followed by a dose increase to 274 mg once daily. The treatment duration was 25 weeks for Study 1 and 13 weeks for Study 2. Of the 100 patients in the safety population described below, 39 patients were treated with GOCOVRI for 24 weeks. The safety data for these trials were pooled.

The most common adverse reactions reported in >10% of GOCOVRI-treated patients and more frequently than on placebo were: hallucinations, dizziness, dry mouth, peripheral edema, constipation, falls, and orthostatic hypotension.

The overall rate of discontinuation because of adverse reactions for GOCOVRI-treated patients was 20%, compared to 8% for placebo-treated patients. Adverse reactions that led to treatment discontinuation in at least 2% of patients were hallucinations (8% GOCOVRI vs. 0% placebo), dry mouth (3% GOCOVRI vs. 0% placebo), peripheral edema (3% GOCOVRI vs. 0% placebo), blurred vision (GOCOVRI 3% vs. 0% placebo), postural dizziness and syncope (GOCOVRI 2% vs. 0% placebo), abnormal dreams (GOCOVRI 2% vs. 1% placebo), dysphagia (GOCOVRI 2% vs. 0% placebo), and gait disturbance (GOCOVRI 2% vs. 0% placebo).

Table 1: Adverse Reactions Reported for ≥3% of Patients Treated with 274 mg GOCOVRI in Study 1 and Study 2 (Pooled Analysis)
Adverse Reactions | GOCOVRI 274 mg N=100 % | Placebo N=98 %
Psychiatric disorders
Hallucinationsa | 21 | 3
Anxietyb | 7 | 3
Insomnia | 7 | 2
Depression/Depressed mood | 6 | 1
Abnormal dreams | 4 | 2
Confusional state | 3 | 2
Nervous system disorders
Dizziness | 16 | 1
Headache | 6 | 4
Dystonia | 3 | 1
Gastrointestinal disorders
Dry mouth | 16 | 1
Constipation | 13 | 3
Nausea | 8 | 3
Vomiting | 3 | 0
General disorders and administration site conditions
Peripheral edema | 16 | 1
Gait disturbance | 3 | 0
Injury, poisoning and procedural complications
Fall | 13 | 7
Contusion | 6 | 1
Infections and infestations
Urinary tract infection | 10 | 5
Skin and subcutaneous tissue disorders
Livedo reticularis | 6 | 0
Pigmentation disorder | 3 | 0
Metabolism and nutrition disorders
Decreased appetite | 6 | 1
Vascular disorders
Orthostatic hypotensionc | 13 | 1
Eye disorders
Blurred vision | 4 | 1
Cataract | 3 | 1
Dry eye | 3 | 0
Musculoskeletal and connective tissue disorders
Joint swelling | 3 | 0
Muscle spasms | 3 | 0
Reproductive system and breast disorders
Benign prostatic hyperplasiad | 6 | 2
Respiratory, thoracic and mediastinal disorders
Cough | 3 | 0
a=Includes visual hallucinations and auditory hallucinations
b=Includes anxiety and generalized anxiety
c=Includes orthostatic hypotension, postural dizziness, syncope, presyncope, and hypotension
d=The denominator is all male patients in the safety population randomized to GOCOVRI (n=54) or placebo (n=57)

Other clinically relevant adverse reactions observed at <3% included somnolence, fatigue, suicide ideation or attempt, apathy, delusions, illusions, and paranoia [see Warnings and Precautions (5.1, 5.2, 5.3)].

Difference in the Frequency of Adverse Reactions by Gender

Adverse reactions reported more frequently in women treated with 274 mg of GOCOVRI (n=46), compared to men (n=54), were: dry mouth (22% women, 11% men), nausea (13% women, 4% men), livedo reticularis (13% women, 0% men), abnormal dreams (9% women, 0% men) and cataracts (7% women, 0% men).

Men treated with 274 mg of GOCOVRI reported the following adverse reactions more frequently than women: dizziness (20% men, 11% women), peripheral edema (19% men, 11% women), anxiety (11% men, 2% women), orthostatic hypotension (7% men, 2% women) and gait disturbance (6% men, 0% women).

Difference in the Frequency of Adverse Reactions by Age

Hallucinations (visual or auditory) were reported in 31% of GOCOVRI-treated patients age 65 years and over (n=52), compared to 10% in patients below the age of 65 years (n=48). Falls were reported in 17% of GOCOVRI-treated patients age 65 and over, compared to 8% of patients below age 65. Orthostatic hypotension was reported in 8% of patients age 65 and over, compared to 2% of patients below age 65.

6.2 Postmarketing Experience

The following adverse reactions have been identified during postapproval use of GOCOVRI. Because these reactions are reported voluntarily from a population of uncertain size, it is not always possible to reliably estimate their frequency or establish a causal relationship to drug exposure.

Nervous System Disorders: Seizure

Vision: Corneal edema

7 DRUG INTERACTIONS

7.1 Other Anticholinergic Drugs

Products with anticholinergic properties may potentiate the anticholinergic-like side effects of amantadine. The dose of anticholinergic drugs or of GOCOVRI should be reduced if atropine-like effects appear when these drugs are used concurrently.

7.2 Drugs Affecting Urinary pH

The pH of the urine has been reported to influence the excretion rate of amantadine. Urine pH is altered by diet, drugs (e.g., carbonic anhydrase inhibitors, sodium bicarbonate), and clinical state of the patient (e.g., renal tubular acidosis or severe infections of the urinary tract).

Since the excretion rate of amantadine increases rapidly when the urine is acidic, the administration of urine acidifying drugs may increase the elimination of the drug from the body. Alterations of urine pH towards the alkaline condition may lead to an accumulation of the drug with a possible increase in adverse reactions. Monitor for efficacy or adverse reactions under conditions that alter the urine pH to more acidic or alkaline, respectively.

7.3 Live Attenuated Influenza Vaccines

Because of its antiviral properties, amantadine may interfere with the efficacy of live attenuated influenza vaccines. Therefore, live vaccines are not recommended during treatment with GOCOVRI. Inactivated influenza vaccines may be used, as appropriate.

7.4 Alcohol

Concomitant use with alcohol is not recommended, as it may increase the potential for CNS effects such as dizziness, confusion, lightheadedness, and orthostatic hypotension [see Warnings and Precautions (5.4)] , and may result in dose-dumping [see Clinical Pharmacology (12.3)] .

8 USE IN SPECIFIC POPULATIONS

8.1 Pregnancy

Risk Summary

There are no adequate data on the developmental risk associated with use of amantadine in pregnant women. Animal studies suggest a potential risk for fetal harm with amantadine. In mice and rats, adverse developmental effects (embryolethality, increased incidence of malformations, and reduced fetal body weight) were observed when amantadine was administered to pregnant animals at clinically relevant doses [see Data].

In the U.S. general population, the estimated background risk of major birth defects and miscarriage in clinically recognized pregnancies is 2-4% and 15-20%, respectively. The background risk for major birth defects and miscarriage in patients with Parkinson's disease is unknown.

Data

Animal Data

The effects of amantadine on development have not been tested in studies conducted in animals using currently recommended methodology; however, developmental toxicity studies of amantadine have been reported in the published literature.

In mice, oral administration of amantadine (0, 10, or 40 mg/kg/day) to pregnant animals during organogenesis (gestation days 7-12) resulted in embryolethality and reduced fetal body weight at the highest dose tested, which was associated with maternal toxicity. The no-effect dose for developmental toxicity in mice (10 mg/kg/day) is less than the recommended human dose (RHD) of 274 mg/day, based on body surface area (mg/m^2).

In rats, oral administration of amantadine (0, 40 or 120 mg/kg/day) to pregnant animals during organogenesis (gestation days 7-12) resulted in embryolethality and reduced fetal body weight at the highest dose. The no-effect dose for developmental toxicity in this study (40 mg/kg/day) is approximately equal to the RHD on a mg/m^2basis.

In another study in pregnant rats, oral administration of amantadine during organogenesis (gestation days 7-14) resulted in an increase in visceral and skeletal malformations at oral doses of 50 and 100 mg/kg/day. The no-effect dose for teratogenicity in this study (37 mg/kg/day) is approximately equal to the RHD on a mg/m^2basis.

Evaluation of parturition, lactation, and post-natal development in a limited number of litters from the mouse and rat studies described above revealed reductions in live litter size and pup weights at birth at 40 mg/kg/day in mice and 120 mg/kg/day in rats.

8.2 Lactation

Risk Summary

Amantadine is excreted into human milk, but amounts have not been quantified. There is no information on the risk to a breastfed infant.

Amantadine may alter breast milk production or excretion [see Data].

The developmental and health benefits of breastfeeding should be considered along with the mother's clinical need for GOCOVRI and any potential adverse effects on the breastfed infant from GOCOVRI or from the underlying maternal condition.

Data

In published studies, amantadine reduced serum prolactin levels and the symptoms of galactorrhea in patients taking neuroleptic drugs. The effect of amantadine on milk supply has not been evaluated in nursing mothers.

8.4 Pediatric Use

The safety and effectiveness of GOCOVRI in pediatric patients have not been established.

8.5 Geriatric Use

The majority of people with Parkinson's disease are 65 years and older. In Phase 3 clinical trials, the mean age of patients at study entry was 65 years. Of the total number of patients in clinical studies of GOCOVRI, 46% were less than 65 years of age, 39% were 65-74 years of age, and 15% were 75 years of age or older.

Hallucinations and falls occurred more frequently in patients 65 years of age or older, compared to those less than 65 years of age [see Adverse Reactions (6.1)].

No dose adjustment is recommended on the basis of age. GOCOVRI is known to be substantially excreted by the kidney, and the risk of adverse reactions may be greater in patients with impaired renal function. Because elderly patients are more likely to have decreased renal function, care should be taken in dose selection, and it may be useful to monitor renal function [see Dosage and Administration (2.3)].

8.6 Renal Impairment

GOCOVRI is contraindicated for use in patients with end-stage renal disease (creatinine clearance values lower than 15 mL/min/1.73 m^2).

For patients with moderate renal impairment (creatinine clearance between 30 and 59 mL/min/1.73 m^2), a 50% dose reduction of GOCOVRI dosage to a starting daily dose of 68.5 mg daily at bedtime for a week, to a maximum dosage of 137 mg daily at bedtime is recommended.

For patients with severe renal impairment (creatinine clearance between 15 and 29 mL/min/1.73 m^2), a daily dose of 68.5 mg at bedtime is the recommended initial and maximum dosage [see Dosage and Administration (2.3)] .

Creatinine clearance values are estimated by the Modification of Diet in Renal Disease (MDRD) method.

10 OVERDOSAGE

Deaths have been reported from overdose with amantadine. The lowest reported acute lethal dose was 1 gram of amantadine hydrochloride (equivalent to 0.8 g amantadine). Acute toxicity may be attributable to the anticholinergic effects of amantadine. Drug overdose has resulted in cardiac, respiratory, renal, or central nervous system toxicity. Pulmonary edema and respiratory distress (including adult respiratory distress syndrome, ARDS) have been reported with amantadine; renal dysfunction, including increased BUN and decreased creatinine clearance, can occur.

Central nervous system effects that have been reported with overdose include agitation, aggressive behavior, hypertonia, hyperkinesia, ataxia, tremor, disorientation, depersonalization, fear, delirium, psychotic reactions, lethargy, and coma. Seizures may be exacerbated in patients with prior history of seizure disorders. Hyperthermia has occurred with amantadine overdose.

For acute overdosing, general supportive measures should be employed along with immediate gastric decontamination if appropriate. Give intravenous fluids if necessary. The excretion rate of amantadine increases with acidification of urine, which may increase the elimination of the drug. Monitor patients for arrhythmias and hypotension. Electrocardiographic monitoring may be needed after ingestion because arrhythmias have been reported after overdose, including arrhythmias with fatal outcomes. Adrenergic agents, such as isoproterenol, in patients with an amantadine overdose has been reported to induce arrhythmias.

Monitor blood electrolytes, urine pH, and urinary output. Although amantadine is not efficiently removed by hemodialysis, this procedure may be useful in the treatment of amantadine toxicity in patients with renal failure.

11 DESCRIPTION

GOCOVRI contains amantadine in an extended-release formulation. The active ingredient in GOCOVRI is amantadine hydrochloride.

The chemical name for amantadine hydrochloride is tricyclo [3.3.1.1^3,7] decan-1-amine, hydrochloride or 1-adamantanamine hydrochloride with the following structural formula:

The molecular formula is C10H17N∙HCl and the molecular weight is 187.71 (g/mol). Amantadine hydrochloride is a white crystalline powder and is non-hygroscopic, practically insoluble in ether, sparingly soluble in methylene chloride, soluble in chloroform, and freely soluble in water, ethanol, and methanol.

GOCOVRI capsules are for oral use. Each capsule contains 68.5 mg or 137 mg amantadine (as 85 mg or 170 mg amantadine hydrochloride, respectively). Capsules also contain the following inactive ingredients: copovidone, ethylcellulose, hypromellose, magnesium stearate, medium-chain triglycerides, microcrystalline cellulose, povidone, and talc in a hard gelatin capsule.

12 CLINICAL PHARMACOLOGY

12.1 Mechanism of Action

The mechanism by which amantadine exerts efficacy in the treatment of dyskinesia in patients with Parkinson's disease or as adjunctive treatment to levodopa/carbidopa in patients with Parkinson's disease experiencing "off" episodes is unknown. Amantadine is a weak uncompetitive antagonist of the NMDA receptor. Amantadine has not been shown to possess direct anticholinergic activity in animal studies; however, it exhibits anticholinergic-like side effects such as dry mouth, urinary retention, and constipation in humans. Amantadine may have direct and indirect effects on dopamine neurons; it exerts dopaminergic-like side effects such as hallucinations and dizziness in humans.

12.2 Pharmacodynamics

The effect of amantadine on QT prolongation was not studied in a dedicated thorough QT study.

Alcohol consumption may increase the potential for CNS effects such as dizziness, confusion, lightheadedness, and orthostatic hypotension [see Drug Interactions (7.4)] .

12.3 Pharmacokinetics

GOCOVRI is an extended-release formulation. The pharmacokinetics of amantadine from 68.5 mg, 137 mg, and 274 mg of GOCOVRI are dose proportional in healthy subjects.

Absorption

After a single dose bedtime administration of GOCOVRI, the median Tmaxfor plasma amantadine was around 12 hours (range 6-20 hours). The steady-state concentrations of GOCOVRI were achieved 4 days after the dose initiation. The steady-state total exposures (AUC0-tau) were 20-30% higher than after single dose, suggesting an accumulation ratio of 1.2-1.3.

Effect of Food

A single dose crossover study of GOCOVRI established the lack of effect of high-fat, high-calorie meal on plasma amantadine pharmacokinetics; additionally, administration of entire capsule contents sprinkled on applesauce also did not affect plasma amantadine pharmacokinetics.

Distribution

The volume of distribution determined after the intravenous administration of amantadine to 15 healthy subjects was 3 to 8 L/kg, suggesting potential extravascular distribution. Amantadine is approximately 67% bound to plasma proteins over a concentration range of 0.1 to 2.0 µg/mL.

Elimination

In a study with healthy volunteers after oral administration, the apparent plasma clearance of amantadine was estimated to be 0.27 ± 0.094 L/hr/kg (range 0.13 to 0.57 L/hr/kg). Amantadine is primarily excreted unchanged in the urine, and in a study of six healthy volunteers, the ratio of amantadine renal clearance to apparent plasma clearance was 0.79 ± 0.17 (mean ± SD). The mean plasma amantadine half-life at steady-state was approximately 16 hours.

Metabolism

Eight metabolites of amantadine have been identified in human urine. One metabolite, an N-acetylated compound, was quantified in human urine and accounted for 0-15% of the administered dose in multiple studies. The contribution of this metabolite to efficacy or toxicity is not known.

Excretion

Amantadine is primarily excreted unchanged in the urine by both glomerular filtration and tubular secretion.

Specific Population

Male/Female Patients

In an integrated analysis of five studies in healthy volunteers (n=147), the mean total amantadine clearance following administration of GOCOVRI, adjusted for body weight in kilograms, was 1.2 fold higher in males compared to females (95% CI: 1.1, 1.3, P=0.007). No dose adjustment by gender is warranted.

Renal Impairment

The renal clearance of amantadine is significantly lower in adult patients with moderate or severe renal impairment, compared to healthy adults. Since the renal pathway is a major elimination pathway, impairment in renal function can result in significant accumulation in the plasma, warranting dose adjustment. The impact of renal impairment on dose adjustment was not investigated in a dedicated study.

Based on PK simulations, the range of the total exposures (AUC0-tau) in subjects with normal renal function (creatinine clearance >90 mL/min/1.73 m^2) or mild renal impairment (creatinine clearance between 60 and 89 mL/min/1.73 m^2) were comparable for the same dosing regimen. However, patients with moderate renal impairment (creatinine clearance between 30 and 59 mL/min/1.73 m^2) had higher exposures relative to patients with normal renal function or mild renal impairment. Severe renal impairment (creatinine clearance between 15 and 29 mL/min/1.73 m^2) resulted in even higher total exposures. Dosage adjustment is recommended in patients with moderate and severe renal impairment [see Use in Special Populations (8.6) and Dosage and Administration (2.3)]. GOCOVRI is contraindicated in patients with end stage renal disease (creatinine clearance less than 15 mL/min/1.73 m^2).

Amantadine is inefficiently removed by hemodialysis.

Drug Interaction Studies

The in vitro dissolution-release profiles showed 52% drug release after 45 minutes, and up to 95% after 2 hours, at concentrations of 40% alcohol/0.1N HCl.

In vitro studies indicate that amantadine has negligible or no inhibitory activity against cellular transporters (P-gp, BCRP, MATE2-K, OAT1, OAT3, OATP1B1, and OATP1B3) at plasma concentrations observed in patients with Parkinson's disease on a GOCOVRI 274 mg dose.

In vitro studies in MDCK-II cells demonstrated that amantadine is not a substrate of the anionic transporters OAT1 or OAT3, or the cationic transporter MATE2-K. Amantadine was a poor substrate of the cationic transporters OCT2 and MATE1. Renal elimination of amantadine may be mediated in part by one or more organic cation transporters independent of OCT2. An in vivo study demonstrated that quinidine, a known organic cation transporter inhibitor, reduced amantadine clearance by approximately 33% in humans. The clinical significance is unknown. In vitro studies show that amantadine does not significantly inhibit the enzyme activity of drug metabolizing cytochrome P450 isoforms (CYP1A2, 2B6, 2C19, 2C8, 2C9, 2D6, 2E1, 3A4, and 3A5).

13 NONCLINICAL TOXICOLOGY

13.1 Carcinogenesis, Mutagenesis, Impairment of Fertility

Carcinogenesis

Animal studies designed to evaluate the carcinogenic potential of amantadine have not been conducted.

Mutagenesis

Amantadine was negative for genotoxicity in in vitro (Ames and mammalian cell [Chinese Hamster ovary and human peripheral blood lymphocytes]) assays in the presence or absence of metabolic activation and in an in vivo mouse bone marrow micronucleus assay.

Impairment of Fertility

The effects of amantadine on fertility have not been adequately tested in a study in animals conducted according to current standards. In a reproduction study reported in the literature, oral administration of amantadine to male and female rats at a dose of 32 mg/kg/day resulted in impaired fertility. The no-effect dose for adverse effects on fertility (10 mg/kg/day) is less than the recommended human dose of 274 mg/day on a mg/m^2basis.

14 CLINICAL STUDIES

Overview of Studies

The efficacy of GOCOVRI for the treatment of dyskinesia in patients with Parkinson's disease and for the adjunctive treatment to levodopa/carbidopa in patients with Parkinsons's disease experiencing "off" episodes was assessed in two randomized, double-blind, placebo-controlled efficacy trials: Study 1 and Study 2. Key inclusion criteria in both studies included at least 1 hour of troublesome dyskinesia time during the day and at least mild functional impact because of dyskinesia.

Study 1 was conducted in 121 (modified Intention to Treat (mITT) population) Parkinson's disease patients with dyskinesia in the United States (US) and Canada. The duration of treatment in Study 1 was up to 25 weeks. Study 2 was conducted in 75 (mITT population) patients with dyskinesia in the US, Germany, France, Spain, and Austria. The duration of treatment was 13 weeks.

In both studies, the primary efficacy endpoint was the change in total score of the Unified Dyskinesia Rating Scale (UDysRS) between baseline and Week 12. Key secondary endpoints derived from a Parkinson's disease home diary included changes from baseline to Week 12 in ON time without troublesome dyskinesia and OFF time.

Study Population

In Study 1 and Study 2, the mean age of patients at the time of Parkinson's disease diagnosis was 55 years (range: 29-75 years).

At baseline, patients had a mean UDysRS total score of 40.1 (range: 8-76), a mean duration of ON time without troublesome dyskinesia (Parkinson's disease home diary) of 8.4 hours (range: 0-15.3), and a mean duration of OFF time of 2.8 hours (range: 0-9.5).

Patients in Study 1 and Study 2 were treated with a stable dose of levodopa, with 32% of patients on levodopa monotherapy. Patients were also treated with concomitant dopamine agonists (54%) and/or MAO-B inhibitors (44%).

Study 1

In Study 1, a significant decrease in mean UDysRS total score (reduction in dyskinesia) was observed at Week 12 in patients treated with GOCOVRI, compared with placebo (Table 2).

Study 2

In Study 2, a significant decrease in mean UDysRS total score (reduction in dyskinesia) was observed at Week 12 in patients treated with GOCOVRI, compared with placebo (Table 2).

Table 2: UDysRS Total Score at Week 12 for Study 1 and Study 2
mITT Population |  | Study 1 |  | Study 2
mITT Population |  | Placebo (N=58) | GOCOVRI 274 mg (N=63) | Placebo (N=38) | GOCOVRI 274 mg (N=37)
UDysRS total score, LS Mean (SE) | Change from Baseline | -8.0 (1.64) | -15.9 (1.62) | -6.3 (2.08) | -20.7 (2.20)
UDysRS total score, LS Mean (SE) | Treatment Difference | -7.9 (2.30) |  | -14.4 (3.03)
UDysRS total score, LS Mean (SE) | P-value | 0.0009 |  | <0.0001

In Study 1 and Study 2, there was a significant increase in ON time without troublesome dyskinesia, and a significant decrease in OFF time between baseline and Week 12 in patients treated with GOCOVRI, compared with placebo (Table 3).

Table 3: PD Home Diary Results at Week 12 for Study 1 and Study 2
mITT Population |  | Study 1 |  | Study 2
mITT Population |  | Placebo (N=58) | GOCOVRI 274 mg (N=63) | Placebo (N=38) | GOCOVRI 274 mg (N=37)
ON Time w/o Troublesome Dyskinesia, LS Mean (SE) | Change from Baseline | 0.8 (0.43) | 3.6 (0.43) | 2.1 (0.53) | 4.0 (0.56)
ON Time w/o Troublesome Dyskinesia, LS Mean (SE) | Treatment Difference | 2.7 (0.61) |  | 1.9 (0.78)
ON Time w/o Troublesome Dyskinesia, LS Mean (SE) | P-value | <0.0001 |  | 0.0168
OFF Time, LS Mean (SE) | Change from Baseline | 0.3 (0.26) | -0.6 (0.27) | 0.6 (0.31) | -0.5 (0.34)
OFF Time, LS Mean (SE) | Treatment Difference | -0.9 (0.37) |  | -1.1 (0.46)
OFF Time, LS Mean (SE) | P-value | 0.0171 |  | 0.0199

16 HOW SUPPLIED/STORAGE AND HANDLING

16.1 How Supplied

GOCOVRI is supplied as extended release capsules in the following configurations:

The 68.5 mg capsule is a white opaque size #2 capsule, with black printing of 'ADAMAS' on front and '85' on back of the cap and three black bands printed on body of capsule.

- 60 count bottles NDC# 17772-085-60

The 137 mg capsule is a light blue opaque size #0 capsule, with black printing of 'ADAMAS' on front and '170' on back of the cap and three black bands printed on body of capsule.

- 60 count bottles NDC# 17772-170-60

16.2 Storage and Handling

Store at 20°C to 25°C (68°F to 77°F); excursions permitted to 15°C to 30°C (59°F to 86°F) [see USP Controlled Room Temperature].

17 PATIENT COUNSELING INFORMATION

Advise the patient to read the FDA-approved patient labeling (Patient Information).

Administration

Instruct patients and caregivers that GOCOVRI capsules should be swallowed whole and can be administered with or without food. Alternatively, GOCOVRI capsules may be opened and the contents sprinkled on applesauce; the entire contents should be consumed immediately without chewing [see Dosage and Administration (2.2)] . Advise patients to speak to their healthcare provider before discontinuation of GOCOVRI.

Falling Asleep During Activities of Daily Living

Advise patients that sleepiness and fatigue that have been reported with GOCOVRI and patients treated with Parkinson's disease medications have reported falling asleep while engaged in activities of daily living. These adverse reactions may affect some patients' ability to drive and operate machinery safely [see Warnings and Precautions (5.1)].

Suicidality and Depression

Instruct patients, family members, and caregivers to notify their healthcare provider if depressed mood, depression, changes in behavior or thinking, and suicidal ideation or behavior develop during treatment [see Warnings and Precautions (5.2)].

Hallucinations/Psychotic Behavior

Inform patients and caregivers that hallucinations and paranoia can occur while taking GOCOVRI. Tell patients to report unreal visions, sounds, or sensations or other psychotic behavior to their healthcare provider promptly should they develop [see Warnings and Precautions (5.3)].

Dizziness and Orthostatic Hypotension

An increased incidence of dizziness, orthostatic hypotension, and syncope was observed with administration of GOCOVRI. Caution patients against standing rapidly after sitting or lying down, especially if they have been doing so for prolonged periods and especially at the initiation of treatment with GOCOVRI [see Warnings and Precautions (5.4)] .

Withdrawal-Emergent Hyperpyrexia and Confusion

Advise patients to contact their healthcare provider before stopping GOCOVRI. Tell patients to inform their healthcare provider if they develop withdrawal symptoms such as fever, confusion, or severe muscle stiffness [see Warnings and Precautions (5.5)].

Corneal Edema

Inform patients about the potential for visual changes including vision loss with administration of GOCOVRI. Advise patients to inform their healthcare provider if they develop visual symptoms such as blurred vision, with or without eye pain, or vision loss [see Warnings and Precautions (5.6)].

Impulse Control/Compulsive Disorders

Inform patients of the potential for experiencing intense urges to gamble, increased sexual urges, intense urges to spend money, binge eating, and other intense urges and the inability to control these urges while taking one or more of the medications that increase central dopaminergic tone, that are generally used for the treatment of Parkinson's disease [see Warnings and Precautions (5.7)].

Drug Interactions

Certain medications can cause an interaction with GOCOVRI. Advise patients and/or caregivers to inform their healthcare provider of all the medicines the patient is taking, including over-the-counter medicines, dietary supplements, and herbal products. Inform patients that live influenza vaccines and consumption of alcohol are not recommended during treatment with GOCOVRI [see Drug Interactions (7.1, 7.2, 7.3, 7.4)].

Manufactured for:

Supernus Pharmaceuticals, Inc.
Rockville, MD 20850

RA-GOC-V2

PATIENT INFORMATION

GOCOVRI (goh-KUV-ree)
(amantadine) extended release capsules, for oral use

What is GOCOVRI?

GOCOVRI is a prescription medicine used:

- for the treatment of dyskinesia (sudden uncontrolled movements) in people with Parkinson's disease who are treated with levodopa therapy or levodopa therapy with other medicines that increase the effects of dopamine in the brain.
- with levodopa and carbidopa in people with Parkinson's disease who are having "off" episodes.

It is not known if GOCOVRI is safe and effective in children.

Do not take GOCOVRI if youhave severe kidney problems.

Before you take GOCOVRI, tell your healthcare provider about all of your medical conditions, including if you:

- have kidney problems.
- have daytime sleepiness from a sleep disorder, have unexpected or unpredictable sleepiness or periods of sleep, take a medicine to help you sleep, or take any medicine that makes you drowsy.
- have mental problems, such as suicidal thoughts, depression, or hallucinations.
- have unusual urges including gambling, increased sex drive, compulsive eating, or compulsive shopping.
- drink alcoholic beverages. This may increase your chances of becoming drowsy or sleepy while taking GOCOVRI.
- are pregnant or plan to become pregnant. GOCOVRI may harm your unborn baby.
- are breastfeeding or plan to breastfeed. GOCOVRI can pass into your breastmilk. Talk to your healthcare provider about the best way to feed your baby if you take GOCOVRI.

Tell your healthcare provider about all the medicines you take, including prescription and over-the-counter medicines, vitamins, and herbal supplements.

Especially tell your healthcare provider if you:

- take medicines like sodium bicarbonate.
- have had or are planning to have a live flu (influenza) vaccination (nasal spray). You can receive the influenza vaccination shot but should notget a live influenza vaccine while taking GOCOVRI.

Know the medicines you take. Keep a list of them to show your healthcare provider and pharmacist when you get a new medicine.

How should I take GOCOVRI?

- Take GOCOVRI exactly as your healthcare provider tells you to.
- Start GOCOVRI with 1 capsule at bedtime. Your healthcare provider may change your dose if needed. If your healthcare provider tells you to take 2 capsules, take them together at bedtime.
- Do notstop or change your dose of GOCOVRI before talking with your healthcare provider. Call your healthcare provider if you have symptoms of withdrawal such as fever, confusion, or severe muscle stiffness.
- GOCOVRI may be taken with food or without food.
- Swallow GOCOVRI capsules whole. Do notcrush, chew, or divide.
- GOCOVRI capsules may be opened and sprinkled on applesauce before swallowing. Sprinkle all of the medicine in the capsule on the applesauce. Take all of the medicine right away without chewing.
- If you miss a dose of GOCOVRI, do not take an extra dose. Take your usual dose of GOCOVRI on the next day at bedtime.
- If you have forgotten to take GOCOVRI for several days, contact your healthcare provider.
- Do notdrink alcohol with your dose of GOCOVRI.
- Do notuse GOCOVRI capsules that are damaged or show signs of tampering.
- If you take too much GOCOVRI, call your healthcare provider or go to the nearest hospital emergency room right away.

What should I avoid while taking GOCOVRI?

- Do notdrive, operate machinery, or do other dangerous activities until you know how GOCOVRI affects you.
- Do notdrink alcohol while taking GOCOVRI. It can increase your chances of getting serious side effects.

What are the possible side effects of GOCOVRI?

GOCOVRI may cause serious side effects, including:

- falling asleep during normal activities.You may fall asleep while doing normal activities such as driving a car, talking, or eating while taking GOCOVRI or other medicines that treat Parkinson's disease. You may fall asleep without being drowsy or without warning. This may result in having accidents. Your chances of falling asleep while doing normal activities while taking GOCOVRI are greater if you take other medicines that cause drowsiness. Tell your healthcare provider right away if this happens.
- suicidal thoughts or actions and depression.Some people taking GOCOVRI have had suicidal thoughts, attempted suicide, or have had depression. Tell your healthcare provider if you have new or sudden changes in mood, behaviors, thoughts, or feelings, including thoughts about hurting yourself or ending your life.
- hallucinations.GOCOVRI can cause or worsen hallucinations (seeing or hearing things that are not real) or psychotic behavior. Hallucinations are a serious and common side effect of GOCOVRI. Contact your healthcare provider if you have hallucinations.
- feeling dizzy, faint or light headed, especially when you stand up (orthostatic hypotension). Light headedness or fainting may happen when getting up too quickly from a sitting or lying position especially after long periods of time, when first starting GOCOVRI, or if your dose has been increased. These side effects are serious and common for GOCOVRI. Contact your healthcare provider if you become light headed or faint when standing up.
- blurred vision, eye pain, vision loss.Tell your healthcare provider if you experience changes to your vision.
- unusual urges.Some people taking GOCOVRI get urges to behave in a way unusual for them. Examples of this are an unusual urge to gamble, increased sexual urges, strong urges to spend money, binge eating and the inability to control these urges. If you notice or your family notices that you are developing any unusual behaviors, talk to your healthcare provider.

The most common side effects of GOCOVRI include hallucinations, dizziness, dry mouth, swelling of legs and feet, constipation, a drop in blood pressure when standing, and falls.

These are not all the possible side effects of GOCOVRI. Call your healthcare provider for medical advice about side effects. You may report side effects to FDA at 1-800-FDA-1088.

How should I store GOCOVRI?

- Store GOCOVRI at room temperature between 68°F to 77°F (20°C to 25°C).
- Keep GOCOVRI and all medicines out of the reach of children.

General information about the safe and effective use of GOCOVRI.

Medicines are sometimes prescribed for purposes other than those listed in a Patient Information leaflet. Do not use GOCOVRI for a condition for which it was not prescribed. Do not give GOCOVRI to other people, even if they have the same symptoms that you have. It may harm them. You can ask your pharmacist or healthcare provider for information about GOCOVRI that is written for health professionals.

What are the ingredients in GOCOVRI?

Active ingredient:amantadine hydrochloride

Inactive ingredients:copovidone, ethylcellulose, hypromellose, magnesium stearate, medium chain triglycerides, microcrystalline cellulose, povidone, and talc

Manufactured for: Supernus Pharmaceuticals, Inc., Rockville, MD 20850

For more information, go to www.GOCOVRI.com or call 1-833-223-2627.
RA-GOC-PPI-V2

This Patient Information has been approved by the U.S. Food and Drug Administration

Revised: 02/2026

PRINCIPAL DISPLAY PANEL - 68.5 mg Capsule Bottle Label

60 Capsules
NDC 17772-085-60

GOCOVRI®
(amantadine) extended release capsules

68.5 mg

Rx only

PRINCIPAL DISPLAY PANEL - 137 mg Capsule Bottle Label

60 Capsules
NDC 17772-170-60

GOCOVRI®
(amantadine) extended release capsules

137 mg

Rx only